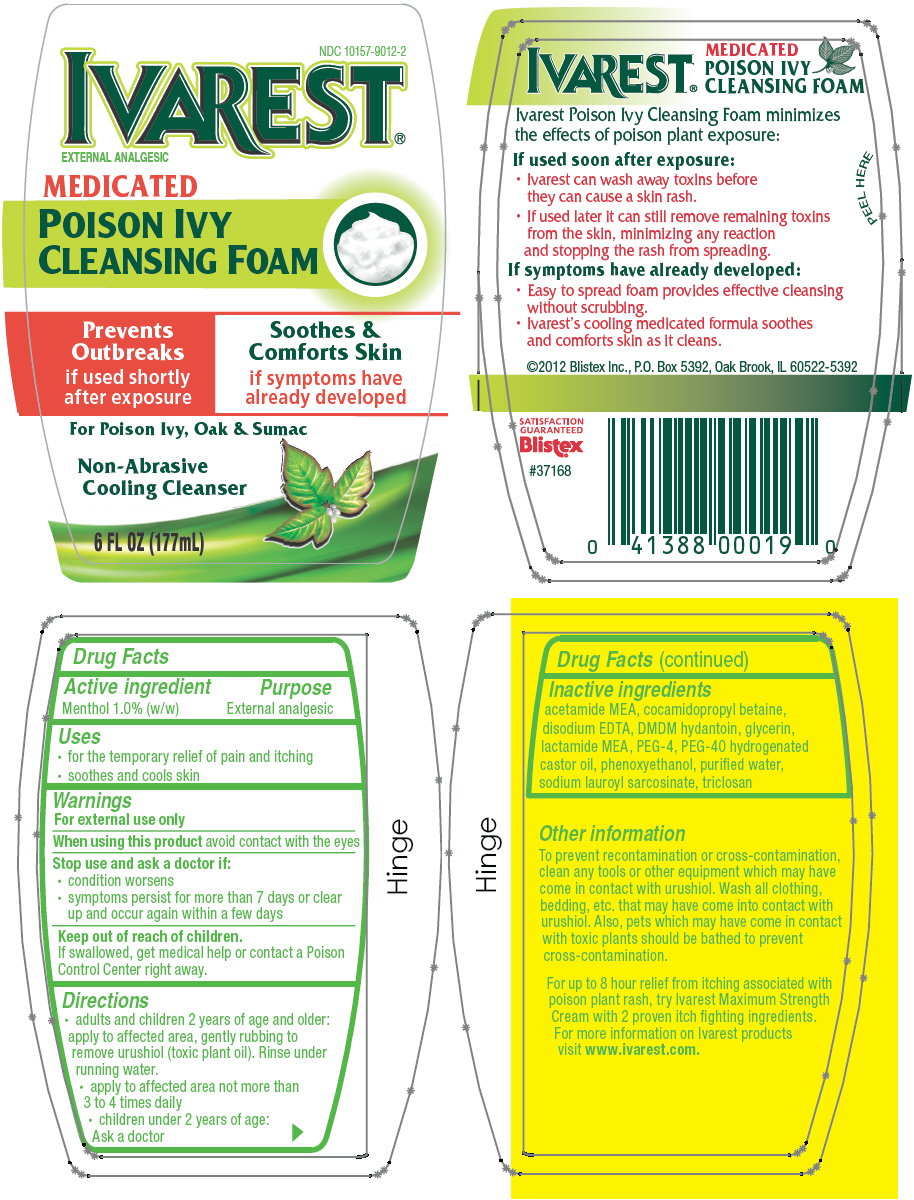 DRUG LABEL: Blistex 
NDC: 10157-9012 | Form: SOAP
Manufacturer: Blistex Inc
Category: otc | Type: HUMAN OTC DRUG LABEL
Date: 20131119

ACTIVE INGREDIENTS: Menthol 1 g/100 mL
INACTIVE INGREDIENTS: WATER; SODIUM LAUROYL SARCOSINATE; COCAMIDOPROPYL BETAINE; ACETIC MONOETHANOLAMIDE; N-LACTOYL ETHANOLAMINE; POLYOXYL 40 HYDROGENATED CASTOR OIL; glycerin; POLYETHYLENE GLYCOL 200; PHENOXYETHANOL; DMDM HYDANTOIN; EDETATE DISODIUM; TRICLOSAN

Blistex
Ivarest® Medicated Poison Ivy Cleansing Foam

Drug Facts

Active ingredient

Menthol 1.0% (w/w)

Purpose

External analgesic

Uses

- for the temporary relief of pain and itching
- soothes and cools skin

Warnings

For external use only

When using this product avoid contact with the eyes

Stop use and ask a doctor if:

- condition worsens
- symptoms persist for more than 7 days or clear up and occur again within a few days

Keep out of reach of children.

If swallowed, get medical help or contact a Poison Control Center right away.

Directions

- adults and children 2 years of age and older: apply to affected area, gently rubbing to remove urushiol (toxic plant oil). Rinse under running water.
- apply to affected area not more than 3 to 4 times daily
- children under 2 years of age: Ask a doctor

Inactive ingredients

acetamide MEA, cocamidopropyl betaine, disodium EDTA, DMDM hydantoin, glycerin, lactamide MEA, PEG-4, PEG-40 hydrogenated castor oil, phenoxyethanol, purified water, sodium lauroyl sarcosinate, triclosan

PRINCIPAL DISPLAY PANEL - 177 mL Bottle Label

NDC 10157-9012-2

IVAREST®
EXTERNAL ANALGESIC

MEDICATED
POISON IVY
CLEANSING FOAM

Prevents
Outbreaks
if used shortly
after exposure

Soothes &
Comforts Skin
if symptoms have
already developed

For Poison Ivy, Oak & Sumac

Non-Abrasive
Cooling Cleanser

6 FL OZ (177mL)